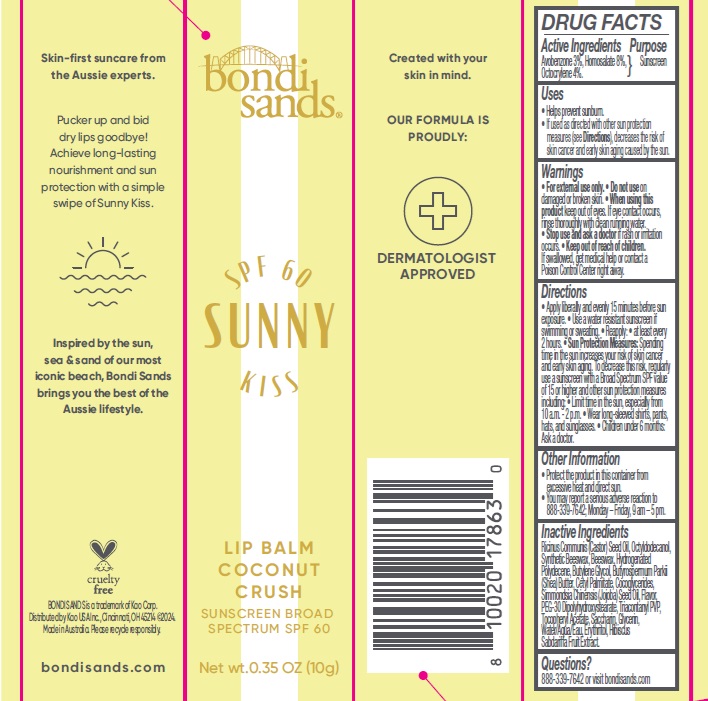 DRUG LABEL: Bondi Sands SPF 60 Sunny Kiss Lip Balm Coconut Crush
NDC: 79950-018 | Form: LIPSTICK
Manufacturer: BONDI SANDS (USA) INC.
Category: otc | Type: HUMAN OTC DRUG LABEL
Date: 20250106

ACTIVE INGREDIENTS: AVOBENZONE 30 mg/1 g; OCTOCRYLENE 40 mg/1 g; HOMOSALATE 80 mg/1 g
INACTIVE INGREDIENTS: HYDROGENATED POLYDECENE (1500 CST); CASTOR OIL; OCTYLDODECANOL; YELLOW WAX; ERYTHRITOL; CETYL PALMITATE; BUTYLENE GLYCOL; COCO-GLYCERIDES; .ALPHA.-TOCOPHEROL ACETATE; SHEA BUTTER; JOJOBA OIL; TRICONTANYL POVIDONE; PEG-30 DIPOLYHYDROXYSTEARATE; SACCHARIN; SYNTHETIC BEESWAX; GLYCERIN; WATER

Bondi Sands SPF 60 Sunny Kiss Lip Balm Coconut Crush

Active Ingredients

Avobenzone 3%

Homosalate 8%

Octocrylene 4%

Purpose

Sunscreen

Uses

- Helps prevent sunburn.
- If used as directed with other sun protection measures (see Directions), decreases the risk of skin cancer and early skin aging caused by the sun.

Warnings

- For external use only.

Do not use

on damaged or broken skin.

When using this product

keep out of eyes. If eye contact occurs, rinse thoroughly with clean running water.

Stop use and ask a doctor

if rash or irritation occurs.

Keep out of reach of children.

If swallowed, get medical help or contact a Poison Control Center right away.

Directions

- Apply liberally and evenly 15 minutes before sun exposure.
- Use a water resistant sunscreen if swimming or sweating.
- Reapply:
- at least every 2 hours.
- Sun Protection Measures: Spending time in the sun increases your risk of skin cancer and early skin aging. To decrease this risk, regularly use a sunscreen with a Broad Spectrum SPF value of 15 or higher and other sun protection measures including:
- Limit time in the sun, especially from 10 a.m. - 2 p.m.
- Wear long-sleeved shirts, pants, hats, and sunglasses.
- Children under 6 months: Ask a doctor.

Other Information

- Protect the product in this container from excessive heat and direct sun.
- You may report a serious adverse reaction to 888-339-7642; Monday – Friday, 9 am – 5 pm.

Inactive Ingredients

Ricinus Communis (Castor) Seed Oil, Octyldodecanol, Synthetic Beeswax, Beeswax, Hydrogenated Polydecene, Butylene Glycol, Butyrospermum Parkii (Shea) Butter, Cetyl Palmitate, Cocoglycerides, Simmondsia Chinensis (Jojoba) Seed Oil, Flavor, PEG-30 Dipolyhydroxystearate, Triacontanyl PVP, Tocopheryl Acetate, Saccharin, Glycerin, Water/Aqua/Eau, Erythritol, Hibiscus Sabdariffa Fruit Extract.

Questions?

888-339-7642 or visit bondisands.com